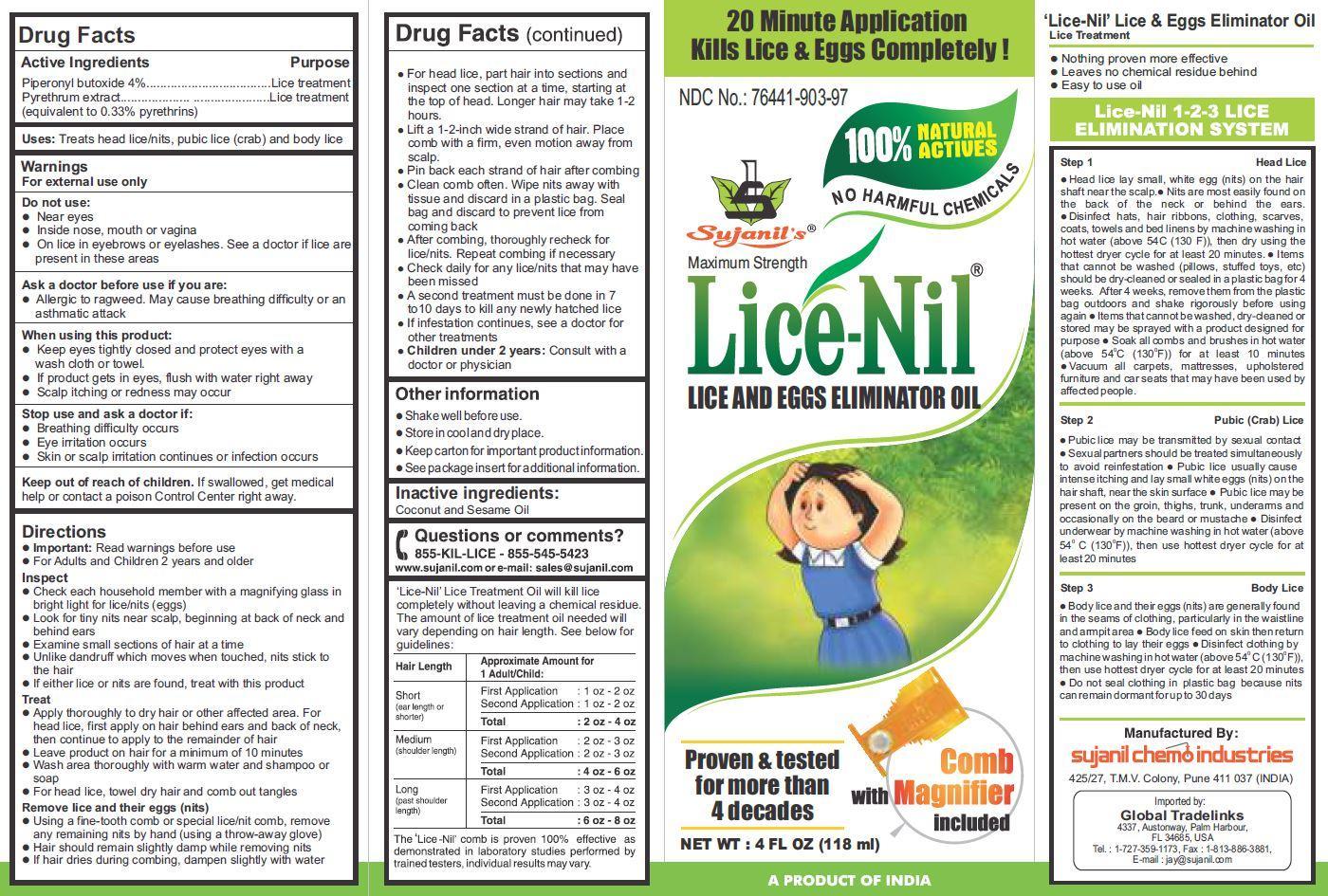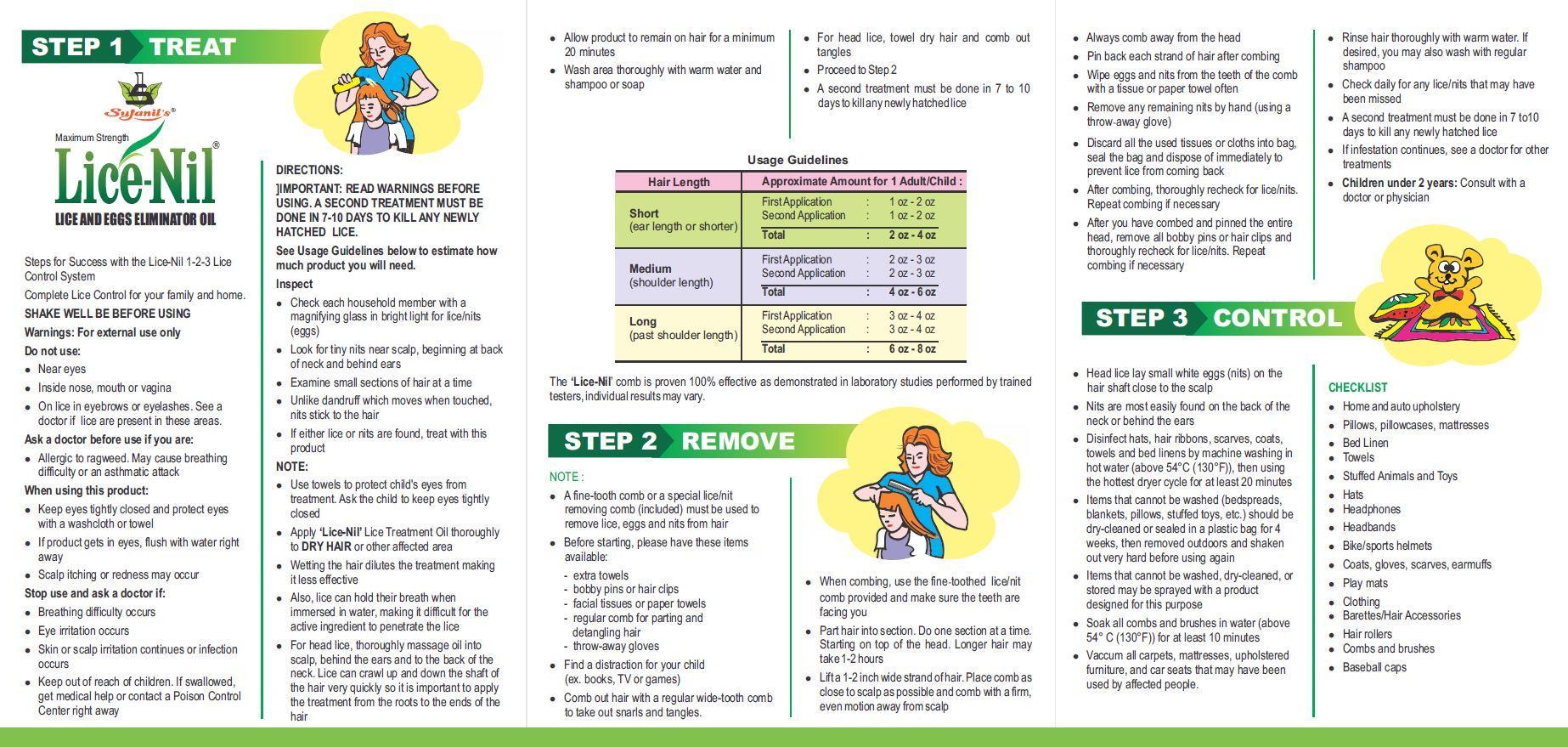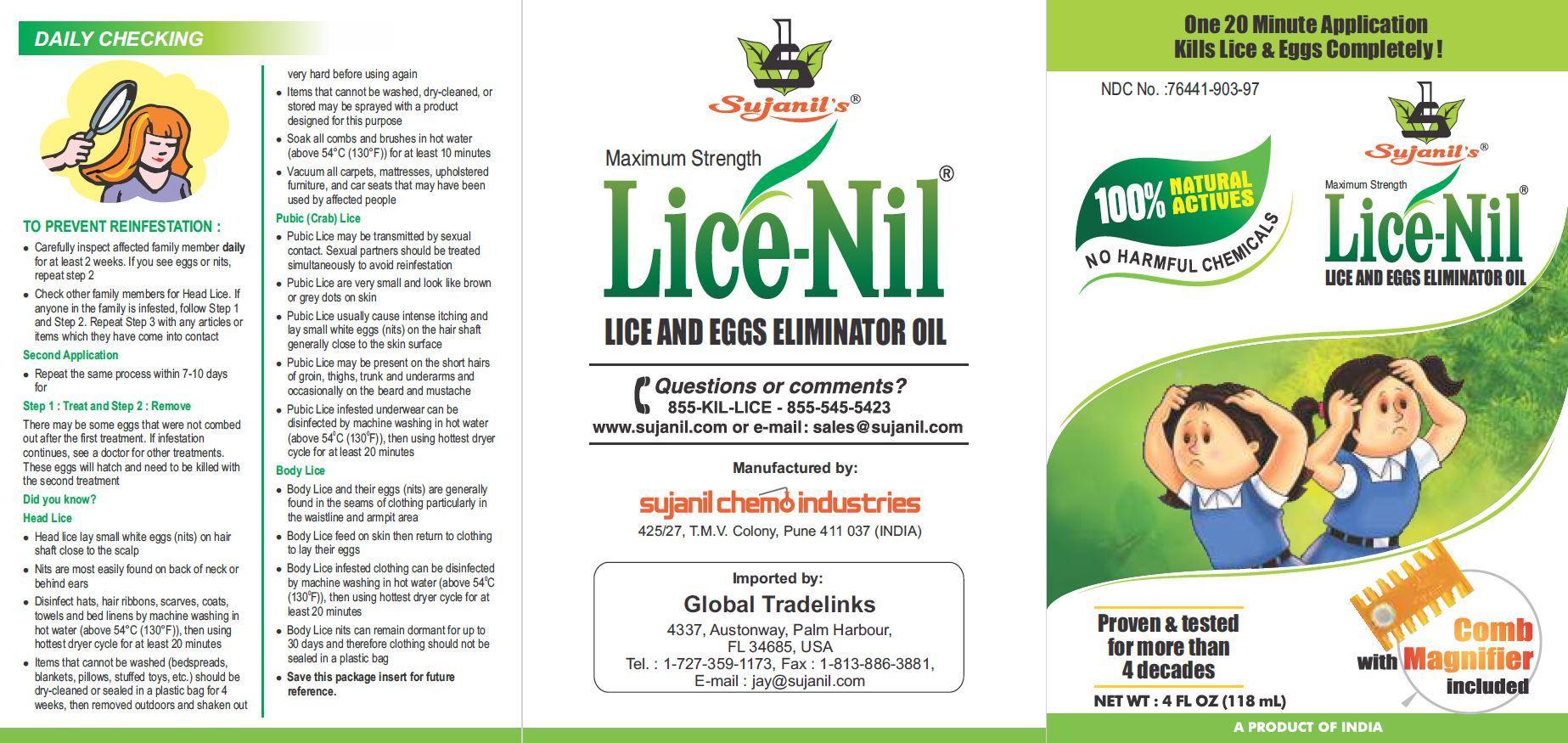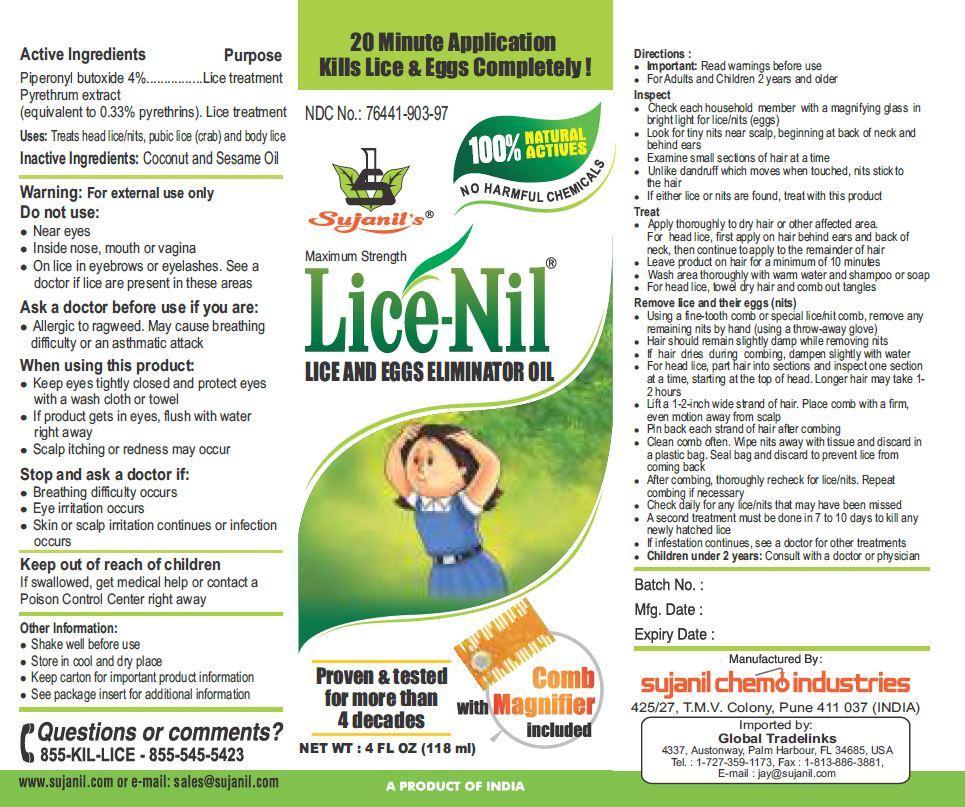 DRUG LABEL: Lice-Nil
NDC: 76441-903 | Form: OIL
Manufacturer: Sujanil Chemo Industries
Category: otc | Type: HUMAN OTC DRUG LABEL
Date: 20141106

ACTIVE INGREDIENTS: PIPERONYL BUTOXIDE 4 g/100 mL; PYRETHRUM EXTRACT 0.33 g/100 mL
INACTIVE INGREDIENTS: SESAME OIL; COCONUT OIL

Lice-Nil Lice & Eggs Killer Oil

Drug Facts

Active ingredients

Piperonyl butoxide 4%

Pyrethrum extract (equivalent to 0.33% pyrethrins)

Purpose

Lice Treatment

Uses

treats head, pubic (crab), and body lice

Warnings

For external use only

Do not use

- near eyes
- inside nose, mouth, or vagina
- on lice in eyebrows or eyelashes. See a doctor if lice are present in these areas.

Ask a doctor before use if you are:

- allergic to ragweed. May cause breathing difficulty or an asthmatic attack.

When using this product

- keep eyes tightly closed and protect eyes with a washcloth or towel.
- if product gets into eyes, flush with water right away.
- scalp itching or redness may occur

Stop use and ask a doctor if

- breathing difficulty occurs
- eye irritation occurs
- skin or scalp irritation continues or infection occurs

Keep out of reach of children. If swallowed, get medical help or contact a Poison Control Center right away.

Directions

Shake well before using

Important: Read warnings before use

adults and children 2 years and over:
Inspect

- check each household member with a magnifying glass in bright light for lice/nits (eggs)
- look for tiny nits near scalp, beginning at back of neck and behind ears
- examine small sections of hair at a time
- unlike dandruff which moves when touched, nits stick to the hair
- if either lice or nits are found, treat with this product

Treat

- apply thoroughly to dry hair or other affected area. For head lice, first apply behind ears and to back of neck.
- allow product to remain for minimum 10 minutes.
- wash area thoroughly with warm water and soap or shampoo.
- for head lice, towel dry hair and comb out tangles.

Remove lice and their eggs (nits)

- use a fine-tooth or special lice/nit comb. Remove any remaining nits by hand (using a throw-away glove).
- hair should remain slightly damp while removing nits
- if hair dries during combing, dampen slightly with water
- for head lice, part hair into sections. Do one section at a time starting on top of the head. Longer hair may take 1 to 2 hours.
- lift a 1- to 2- inch wide strand of hair. Place comb as close to scalp as possible and comb with a firm, even motion away from scalp.
- pin back each strand of hair after combing.
- clean comb often. Wipe nits away with tissue and discard in a plastic bag. Seal bag and discard to prevent lice from coming back.
- after combing, thoroughly recheck for lice/nits. Repeat combing if necessary.
- check daily for any lice/nits that you missed.
- a second treatment must be done in 7 to 10 days to kill any newly hatched lice.
- if infestation continues, see a doctor for other treatments.
- children under 2 years: ask a doctor

Other Information

- shake well before use
- store in cool and dry place
- keep carton for important product information
- see package insert for additional information.

Inactive ingredients

vegetable oils

Questions or comments?
855-KIL-LICE - 855-545-5423
www.sujanil.com or e-mail: sales@sujanil.com

Package Insert

DAILY CHECKING

TO PREVENT REINFESTATION:

- Carefully inspect infested family member daily for at least 2 weeks. If you see eggs or nits, repeat step 2.
- Check other family members for Head Lice. If anyone in the family is infested, follow Step 1 and Step 2. Repeat Step 3 with any articles or items with which they have come in contact.

Second Application

- Repeat the same procedures within 7 - 10 days for

Step 1: Treat and Step 2: Remove

- There may be some eggs that were not combed out after the first treatment. If infestation continues, see a doctor for other treatments. These eggs will hatch and need to be killed with the second treatment.

Did you know?

Head Lice

- Head lice lay small white eggs (nits) on hair shaft close to the scalp
- Nits are most easily found on back of neck or behind ears
- Disinfect hats, hair ribbons, scarves, coats, towels and bed linens by machine washing in hot water (above 54°C (130°F)), then using hottest dryer cycle for at least 20 minutes
- Items that cannot be washed (bedspreads, blankets, pillows, stuffed toys, etc.) should be dry-cleaned or sealed in a plastic bag for 4 weeks, then removed outdoors and shaken out very hard before using again
- Items that cannot be washed, dry-cleaned, or stored may be sprayed with a product designed for this purpose
- Soak all combs and brushes in hot water (above 54°C (130°F)) for at least 10 minutes
- Vacuum all carpets, mattresses, upholstered furniture, and car seats that may have been used by affected people.

Pubic (Crab) Lice

- Pubic Lice may be transmitted by sexual contact. Sexual partners should be treated simultaneously to avoid reinfestation.
- Pubic Lice are very small and look like brown or grey dots on skin.
- Pubic Lice usually cause intense itching and lay small white eggs (nits) on the hair shaft generally close to the skin surface.
- Pubic Lice may be presented on the short hairs of groin, thighs, trunk and underarms and occasionally on the beard and mustache.
- Pubic Lice infested underwear can be disinfected by machine washing in hot water (above 54°C (130°F)), then using hottest dryer cycle for at least 20 minutes.

Body Lice

- Body Lice and their eggs (nits) are generally found in the seams of clothing particularly in waistline and armpit area.
- Body Lice feed on skin then return to clothing to lay their eggs.
- Body Lice infested clothing can be disinfected by machine washing in hot water (above 54°C (130°F)), then using the hottest dryer cycle for at least 20 minutes.
- Body Lice nits can remain dormant for up to 30 days and therefore clothing should not be sealed in a plastic bag
- Save this package insert for future reference.

STEP 1 TREAT

Lice-Nil Lice & Eggs Killer Oil

Steps to Success

with 1-2-3 Lice Control System

Complete Lice Control for your family and home.

SHAKE WELL BEFORE USING

DIRECTIONS: IMPORTANT: READ WARNINGS BEFORE USING. A SECOND TREATMENT MUST BE DONE IN 7-10 DAYS TO KILL ANY NEWLY HATCHED LICE.

Warnings

For external use only

Do not use:

- near eyes,
- inside nose, mouth or vagina,
- on lice in eyebrows or eyelashes. See a doctor if lice are present in these areas

Ask a doctor before use if you are

- allergic to ragweed. May cause breathing difficulty or an asthmatic attack

When using this product

- keep eyes tightly closed and protect eyes with a washcloth or towel
- if product gets in eyes, flush with water right away
- scalp itching or redness may occur

Stop use and ask a doctor if

- breathing difficulty occurs
- eye irritation occurs
- skin or scalp irritation continues or infection occurs
- Keep out of reach of children. if swallowed, get medical help or contact a Poison Control Center right away

See Usage Guidelines below to estimate how much product you will need.

Usage Guidelines
Hair Length | Approximate Amount for 1 Adult/Child:
Short (ear length or shorter) | First Application : 1 oz - 2 oz; Second Application : 1 oz - 2 oz; Total : 2 oz - 4 oz
Medium (shoulder length) | First Application : 2 oz - 3 oz; Second Application : 2 oz - 3 oz; Total : 4 oz - 6 oz
Long (past shoulder length) | First Application : 3 oz - 4 oz; Second Application : 3 oz - 4 oz; Total : 6 oz - 8 oz

Inspect

- check each household member with a magnifying glass in bright light for lice/nits (eggs)
- look for tiny nits near scalp, beginning at back of neck and behind ears
- examine small sections of hair at time
- unlike dandruff which moves when touched, nits stick to the hair
- if either lice or nits are found, treat with this product

NOTE:

- Use towels to protect child's eyes from treatment. Ask the child to keep eyes tightly closed.
- Apply 'Lice-Nil' Lice & Eggs Killer Oil thoroughly to DRY HAIR or other affected area.
- Wetting the hair dilutes the treatment making it less effective.
- Also lice can hold their breath when immersed in water making it difficult for the active ingredient to penetrate the lice
- For head lice, thoroughly massage oil into scalp, behind the ears and to the back of the neck. Lice can crawl up and down the shaft of the hair very quickly so it is important to apply the treatment from the roots to the ends of the hair.
- Allow product to remain for minimum 10 minutes.
- Wash area thoroughly with warm water and soap or shampoo
- For head lice, towel dry hair and comb out tangles
- Proceed to Step 2.
- A second treatment must be done in 7 to 10 days to kill any newly hatched lice.

The 'Licel-Nil' comb is proven 100% effective as demonstrated in laboratory studies performed by trained testers, individual results may vary.

STEP 2 REMOVE

NOTE:

- A fine - toothed come or special lice / nit removing comb (included) must be used to remove lice, eggs, and nits from hair.
- Before starting have on hand:

- extra towels

- bobby pins or hair clips

- facial tissues or paper towels

- regular comb for parting and detangling hair

- throw-away gloves

- Find a distraction for your child (e.g. books, TV, game)
- Comb out hair with a regular wide-tooth comb to take out snarls and tangles.
- When combing, use the fine-toothed lice/nit comb provided and make sure the teeth are facing you.
- Part hair into section. Do one section at a time. Starting on top of the head. Longer hair may take 1 to 2 hours.
- Lift a 1- to 2- inch wide strand of hair. Place comb as close to scalp as possible and comb with a firm, even motion away from scalp.
- Always comb away from the head.
- Pin back each strand of hair after combing.
- Wipe eggs and nits from the teeth of the comb with a tissue or paper towel often.
- Remove any remaining nits by hand (using a throw-away glove)
- Discard all the used tissue or cloths into bag, seal the bag and dispose of immediately to prevent lice from coming back.
- After combing, throughly recheck for lice/nits. Repeat combing if necessary
- After you have combed and pinned the entire head, remove all bobby pins or hair clips and thoroughly recheck for lice/nits. Repeat combing if necessary.
- Rinse hair thoroughly with warm water, If desired, you may also wash with regular shampoo.
- Check daily for any lice/nits that you missed.
- A second treatment must be done in 7 to 10 days to kill any newly hatched lice.
- If infestation continues, see a doctor for other treatments.
- Children under 2 years: Ask a doctor

STEP 3 CONTROL

- Head lice lay small white eggs (nits) on the hair shaft close to the scalp
- Nits are most easily found on the back of the neck or behind the ears
- Disinfect hats, hair ribbons, scarves, coats, towels and bed linens by machine washing in hot water (above 54°C (130°F)), then using the hottest dryer cycle for at least 20 minutes.
- Items that cannot be washed (bedspreads, blankets, pillows, stuffed toys, etc.) should be dry-cleaned or sealed in a plastic bag for 4 weeks, then removed outdoors and shaken out very hard before using again
- Items that cannot be washed, dry-cleaned, or stored may be sprayed with a product designed for this purpose
- Soak all combs and brushes in to water (above 54°C (130°F)) for at least 10 minutes
- Vacuum all carpets, mattresses, upholstered furniture, and car seats that may have been used by affected people.

CHECKLIST

- Home and auto upholstery
- Pillows, pillowcases, mattresses
- Bed Linen
- Towels
- Stuffed animals toys
- Hats
- Headphones
- Headbands
- Bike/sports helmets
- Coats, gloves, scarves, earmuffs
- Pay mats
- Clothing
- Barettes/Hair ornaments
- Hair rollers
- Combs and brushes
- Baseball caps